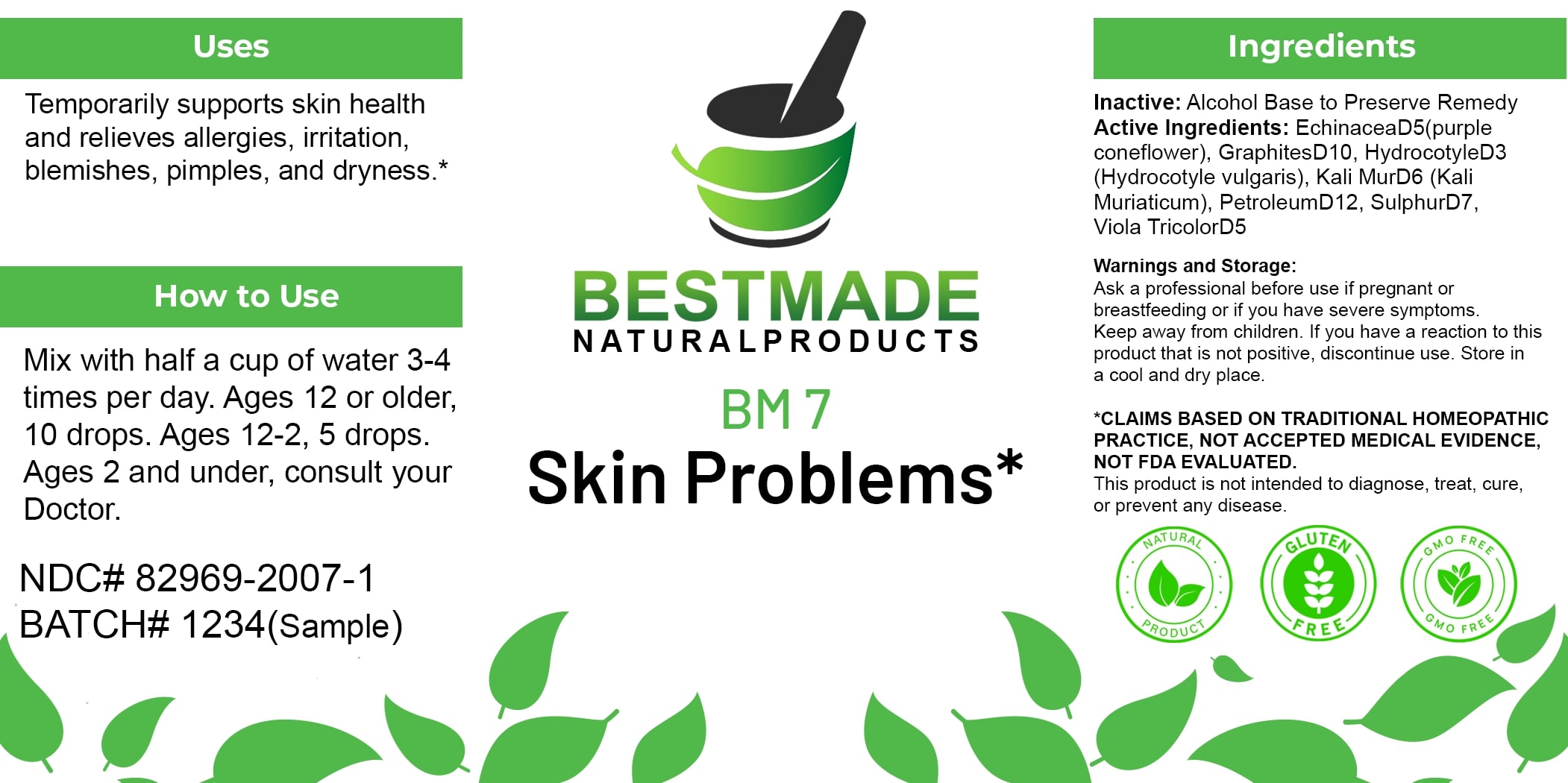 DRUG LABEL: Bestmade Natural Products BM7
NDC: 82969-2007 | Form: LIQUID
Manufacturer: Bestmade Natural Products
Category: homeopathic | Type: HUMAN OTC DRUG LABEL
Date: 20250122

ACTIVE INGREDIENTS: SULFUR 30 [hp_C]/30 [hp_C]; VIOLA TRICOLOR 30 [hp_C]/30 [hp_C]; ECHINACEA ANGUSTIFOLIA 30 [hp_C]/30 [hp_C]; CENTELLA ASIATICA 30 [hp_C]/30 [hp_C]; GRAPHITE 30 [hp_C]/30 [hp_C]; POTASSIUM CHLORIDE 30 [hp_C]/30 [hp_C]; KEROSENE 30 [hp_C]/30 [hp_C]
INACTIVE INGREDIENTS: ALCOHOL 30 [hp_C]/30 [hp_C]

BM7

DOSAGE AND ADMINISTRATION

How to Use

Mix with half a cup of water 3-4 times per day. Ages 12 or older, 10 drops. Ages 12-2, 5 drops. Ages 2 and under, consult your Doctor.

INACTIVE INGREDIENT

Ingredients

Inactive: Alcohol Base to Preserve Remedy

Uses

Temporarily supports skin health and relieves allergies, irritation, blemishes, pimples, and dryness.*

*CLAIMS BASED ON TRADITIONAL HOMEOPATHIC PRACTICE, NOT ACCEPTED MEDICAL EVIDENCE. NOT FDA EVALUATED.

This product is not intended to diagnose, treat, cure, or prevent any disease.

ACTIVE INGREDIENT

Active Ingredients: Echinacea D5 (purple coneflower), Graphites D10, Hydrocotyle D3 (Hydrocotyle vulgaris), Kali Mur D6 (Kali Muriaticum), Petroleum D12, Sulphur D7, Viola Tricolor D5

KEEP OUT OF REACH OF CHILDREN

Warnings and Storage:

Ask a professional before use if pregnant or breastfeeding or if you have severe symptoms. Keep away from children. If you have a reaction to this product that is not positive, discontinue use. Store in a cool and dry place.

Uses

Temporarily supports skin health and relieves allergies, irritation, blemishes, pimples, and dryness.*

*CLAIMS BASED ON TRADITIONAL HOMEOPATHIC PRACTICE, NOT ACCEPTED MEDICAL EVIDENCE. NOT FDA EVALUATED.

This product is not intended to diagnose, treat, cure, or prevent any disease.

Warnings and Storage:

Ask a professional before use if pregnant or breastfeeding or if you have severe symptoms. Keep away from children. If you have a reaction to this product that is not positive, discontinue use. Store in a cool and dry place.

*CLAIMS BASED ON TRADITIONAL HOMEOPATHIC PRACTICE, NOT ACCEPTED MEDICAL EVIDENCE. NOT FDA EVALUATED.

This product is not intended to diagnose, treat, cure, or prevent any disease.

Entire package label